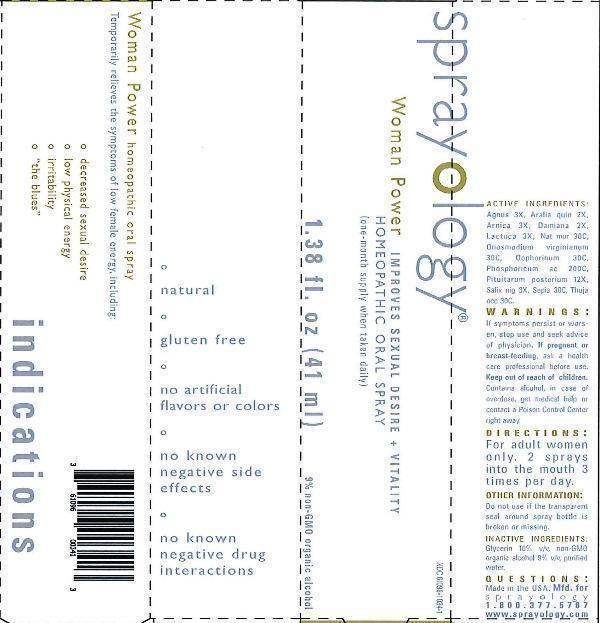 DRUG LABEL: Sprayology Woman Power
NDC: 61096-1034 | Form: LIQUID
Manufacturer: Eight and Company
Category: homeopathic | Type: HUMAN OTC DRUG LABEL
Date: 20160729

ACTIVE INGREDIENTS: CHASTE TREE 3 [hp_X]/41 mL; AMERICAN GINSENG 2 [hp_X]/41 mL; ARNICA MONTANA 3 [hp_X]/41 mL; TURNERA DIFFUSA LEAFY TWIG 2 [hp_X]/41 mL; LACTUCA VIROSA 3 [hp_X]/41 mL; SODIUM CHLORIDE 30 [hp_C]/41 mL; ONOSMODIUM VIRGINIANUM WHOLE 30 [hp_C]/41 mL; SUS SCROFA OVARY 30 [hp_C]/41 mL; PHOSPHORIC ACID 200 [hp_C]/41 mL; SUS SCROFA PITUITARY GLAND 12 [hp_X]/41 mL; SALIX NIGRA BARK 3 [hp_X]/41 mL; SEPIA OFFICINALIS JUICE 30 [hp_C]/41 mL; THUJA OCCIDENTALIS LEAFY TWIG 30 [hp_C]/41 mL
INACTIVE INGREDIENTS: GLYCERIN; ALCOHOL; WATER

Sprayology Woman Power

ACTIVE INGREDIENT

Active Ingredients: Agnus castus 3X, Aralia quinquefolia 2X, Arnica montana 3X, Damiana 2X, Lactuca virosa 3X, Natrum muriaticum 30C, Onosmodium virginianum 30C, Oophorinum 30C, Phosphoricum acidum 200C, Pituitarum posterium 12X, Salix nigra 3X, Sepia 30C, Thuja occidentalis 30C.

WARNINGS

Warnings: If symptoms persist or worsen, stop use and seek advice of physician. If pregnant or breast-feeding, ask a health care professional before use. Keep out of reach of children. Contains alcohol, in case of overdose, get medical help or contact a Poison Control Center right away.

Keep out of reach of children.

Directions:

- For adult women only. 2 sprays into the mouth 3 times per day.

PURPOSE

Temporarily relieves the symptoms of low female energy, including:

- decreased sexual desire
- low physical energy
- irritability
- "the blues"

Other Information: Do not use if the transparent seal around spray bottle is broken or missing.

INACTIVE INGREDIENT

Inactive Ingredients: Glycerin 10% v/v, non-GMO organic alcohol 9% v/v, purified water.

INDICATIONS AND USAGE

Temporarily relieves the symptoms of low female energy, including:

º decreased sexual desire

º low physical energy

º irritability

º "the blues"

° natural

° gluten free

° no artificial flavors or colors

° no known negative side effects

° no known negative drug interactions